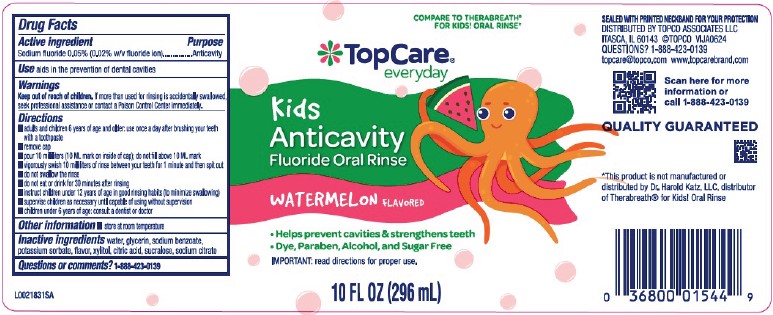 DRUG LABEL: Anticavity fluoride rinse
NDC: 76162-838 | Form: MOUTHWASH
Manufacturer: Topco Associates LLC
Category: otc | Type: HUMAN OTC DRUG LABEL
Date: 20260213

ACTIVE INGREDIENTS: SODIUM FLUORIDE 0.2 mg/1 mL
INACTIVE INGREDIENTS: WATER; GLYCERIN; SODIUM BENZOATE; POTASSIUM SORBATE; XYLITOL; CITRIC ACID MONOHYDRATE; SUCRALOSE; SODIUM CITRATE, UNSPECIFIED FORM

Top Care 838.000/838AB
Kids Anticavity Fluoride Oral Rinse {Wonderful Watermelon}

Active ingredient

Sodium fluoride 0.05% (0.02% w/v fluoride ion)

Purpose

Anticavity

Use

aids in the prevention of dental cavities

Warning

For this product

Keep out of reach of children.

If more than used for rinsing is accidentally swallowed, seek professional assistance or contact a Poison Control Center immediately.

Directions

- adults and children 6 years of age and older: use once a day after brushing your teeth with a toothpaste
- remove cap
- pour 10 milliliters (10 ML mark on inside of cap); do not fill above 10 ML mark
- vigorously swish 10 milliliters of rinse between your teeth for 1 minute and then spit out
- do not swallow the rinse
- do not eat or drink for 30 minutes after rinsing
- instruct children under 12 years of age in good rinsing habits (to minimize swallowing)
- supervise children as necessary until capable of using without supervision
- children under 6 years of age: consult a dentist or doctor

Other information

- store at room temperature

Inactive ingredients

water, glycerin, sodium benzoate, potassium sorbate, flavor, xylitol, citric acid, sucralose, sodium citrate

Questions or comments?

1-888-423-0139

TAMPER EVIDENT STATEMENT

SEALED WITH PRINTED NECKBAND FOR YOUR PROTECTION

ADVERSE REACTIONS

DISTRIBUTED BY TOPCO ASSOCIATES LLC

ITASCA, IL 60143 ©TOPCO VIJA0624

QUESTIONS? 1-888-423-0139

topcare@topco.com www.topcarebrand.com

Scan here for more information or call 1-888-423-0139

QUALITY GUARANTEED

Disclaimer

*This product is not manufactured or distributed by Dr. Harold Katz, LLC., distributor of TheraBreath®for Kids! Oral Rinse

PRINCIPAL DISPLAY PANEL

COMPARE TO THERABREATH® FOR KIDS! ORAL RINSE*

TopCare®

everyday

Kids Anticavity

Fluoride Oral Rinse

Watermelon Flavored

- Helps prevent cavites & strengthens teeth
- Dye, Paraben, Alcohol, and Sugar Free

IMPORTANT: read directions for proper use.

10 FL OZ (296 mL)